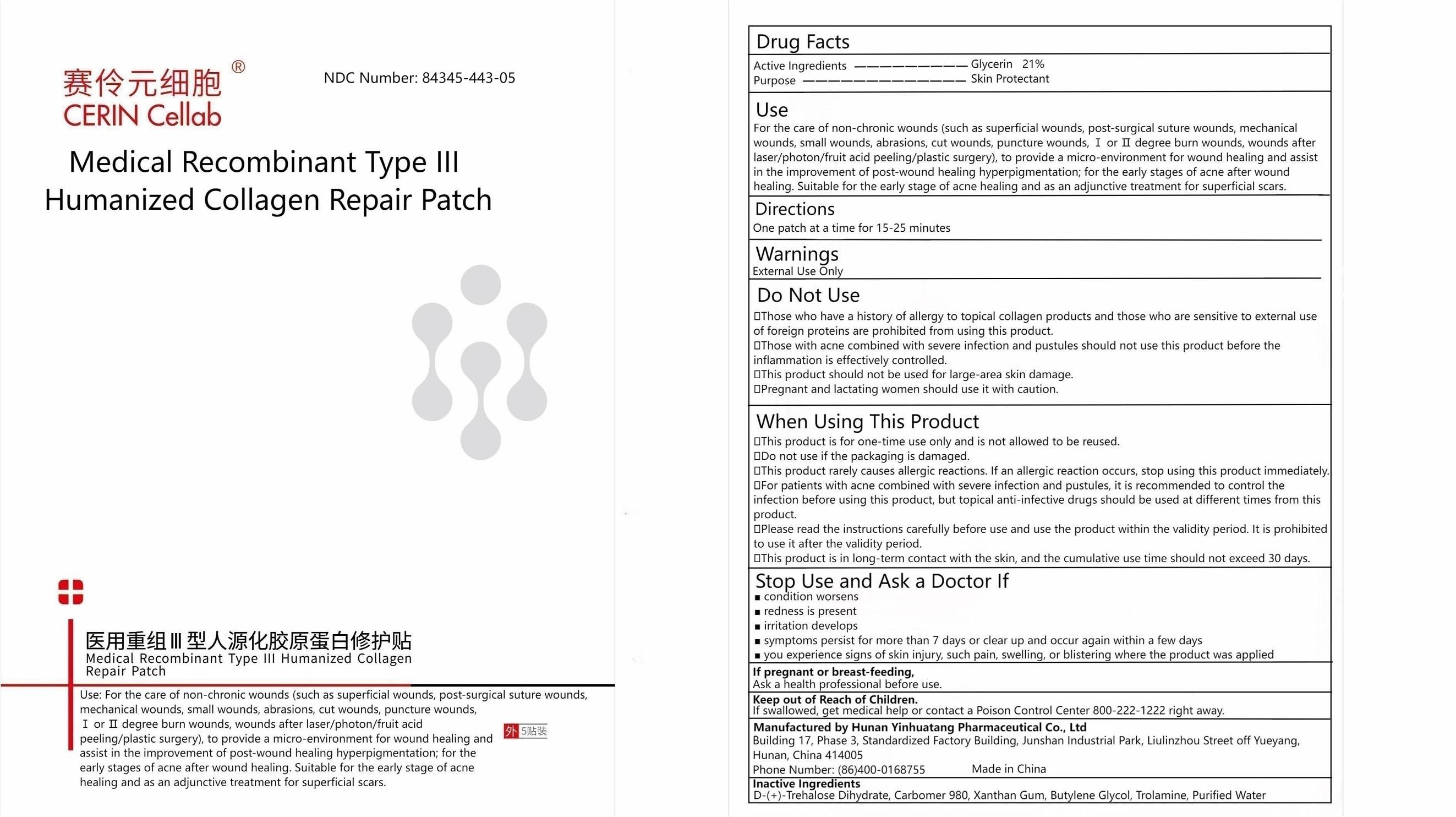 DRUG LABEL: Medical Recombinant type III Humanized Collagen Repair Patch
NDC: 84345-443 | Form: PATCH
Manufacturer: Hunan Yinhuatang Pharmaceutical Technology Co., Ltd
Category: otc | Type: HUMAN OTC DRUG LABEL
Date: 20241213

ACTIVE INGREDIENTS: GLYCERIN 21 g/100 g
INACTIVE INGREDIENTS: TREHALOSE DIHYDRATE; CARBOMER 980; XANTHAN GUM; BUTYLENE GLYCOL; TROLAMINE; WATER

Hunan Yinhuatang Pharmaceutical Technology Co., Ltd

Active Ingredients

Glycerin 21%

Purpose

Skin Protectant

Use

For the care of non-chronic wounds (such as superficial wounds, post-surgical suture wounds, mechanical wounds, small wounds, abrasions, cut wounds, puncture wounds, Ⅰ or Ⅱ degree burn wounds, wounds after laser/photon/fruit acid peeling/plastic surgery), to provide a micro-environment for wound healing and assist in the improvement of post-wound healing hyperpigmentation; for the early stages of acne after wound healing. Suitable for the early stage of acne healing and as an adjunctive treatment for superficial scars.

Directions

One patch at a time for 15-25 minutes.

Warnings

External Use Only

Do Not Use

- Those who have a history of allergy to topical collagen products and those who are sensitive to external use of foreign proteins are prohibited from using this product.
- Those with acne combined with severe infection and pustules should not use this product before the inflammation is effectively controlled.
- This product should not be used for large-area skin damage.
- Pregnant and lactating women should use it with caution.

When Using This Product

- This product is for one-time use only and is not allowed to be reused.
- Do not use if the packaging is damaged.
- This product rarely causes allergic reactions. If an allergic reaction occurs, stop using this product immediately.
- For patients with acne combined with severe infection and pustules, it is recommended to control the infection before using this product, but topical anti-infective drugs should be used at different times from this product.
- Please read the instructions carefully before use and use the product within the validity period. It is prohibited to use it after the validity period.
- This product is in long-term contact with the skin, and the cumulative use time should not exceed 30 days.

Stop Use and Ask A Doctor If

■ condition worsens
■ redness is present
■ irritation develops
■ symptoms persist for more than 7 days or clear up and occur again within a few days
■ you experience signs of skin injury, such pain, swelling, or blistering where the product was applied

If pregnant or breast-feeding,

Ask a health professional before use.

Keep out of Reach of Children.

If swallowed, get medical help or contact a Poison Control Center 800-222-1222 right away.

Manufactured by Hunan Yinhuatang Pharmaceutical Co., Ltd. Building 17, Phase 3, Standardized Factory Building, Junshan Industrial Park, Liulinzhou Street Off Yueyang, Hunan, China 414005Phone Number: (86)400-0168755

Made in China

Inactive Ingredients

D-(+)-Trehalose Dihydrate, Carbomer 980, Xanthan Gum, Butylene Glycol, Trolamine, Purified Water